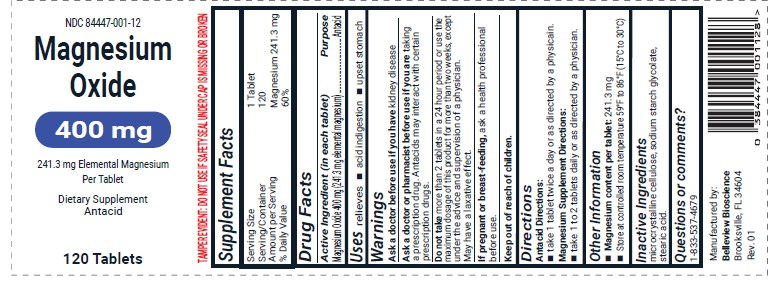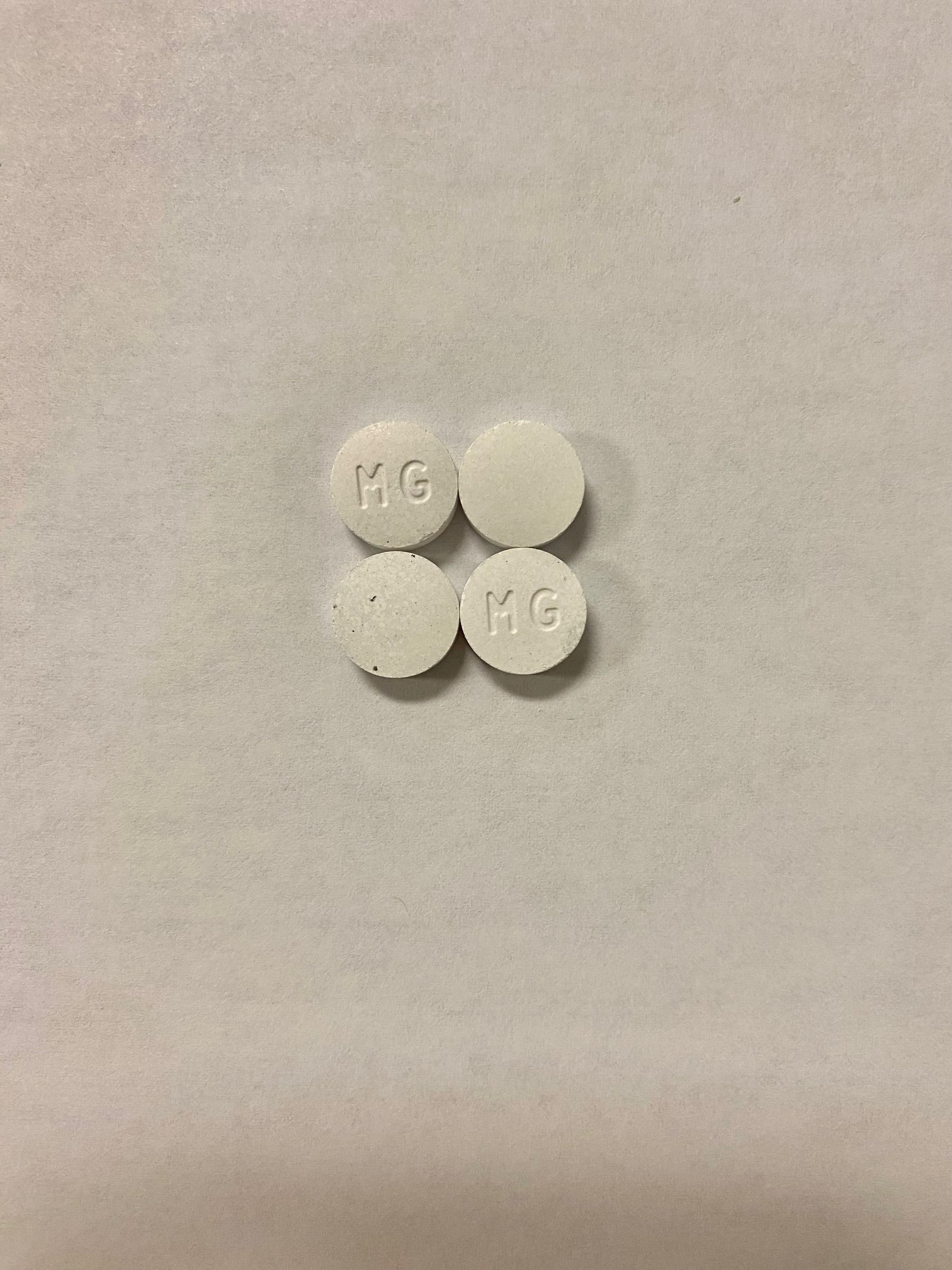 DRUG LABEL: Magnesium Oxide
NDC: 84447-001 | Form: TABLET
Manufacturer: Belleview Biosciences
Category: otc | Type: HUMAN OTC DRUG LABEL
Date: 20250401

ACTIVE INGREDIENTS: MAGNESIUM OXIDE 241.3 mg/1000 mg
INACTIVE INGREDIENTS: SODIUM STARCH GLYCOLATE TYPE A POTATO; STEARIC ACID; CELLULOSE, MICROCRYSTALLINE

Magnesium Oxide

DRUG FACTS

Active Ingredient (in each tablet) | Purpose
Magnesium Oxide 400mg (241.3mg elemental magnesium | Antacid

Purpose

Antacid

Uses

relieves

- acid indigestion
- upset stomach

Warnings

Ask a doctor before use if:

* you have kidney disease

* you are taking a prescription drug (antacids may interact with certain prescription drugs)

* you are pregnant or breast feeding

Ask a doctor or pharmacist before use if you are taking a prescription drug. Antacids may interact with certain prescription drugs.

Keep out of reach of children

PREGNANCY OR BREAST FEEDING

If pregnant or breast-feeding, ask a health professional before use.

Do Not Take

more than 2 tablets in a 24 hour period or use the maximum dosage of this product fo more than two weeks, except under the advice and supervision of a physican. May have a laxative effect.

Dosage and Administration

Antacid Directions

Take 1 Tablet twice a day or as directed by a physicain.

Magnesium Supplement Directions:

Take 1 to 2 Tablets daily or as directed by a physician.

Other Information

- Magnesium content per tablet: 241.3mg
- Store at controlled room temperature 59oF to 86oF (15oC to 30oC)

INACTIVE INGREDIENT

Microcrystaline Cellulose,

Sodium Starch Glycolate,

Stearic Acid

Questions of Comments?

1-833-537-4679

NDC 84447-001-12

Belleview Biosciences LLC

15431 Flight Path Dr, Brooksville, FL 34604

Magnesium Oxide 400mg

NDC 84447-001-12

120 Count Tablet